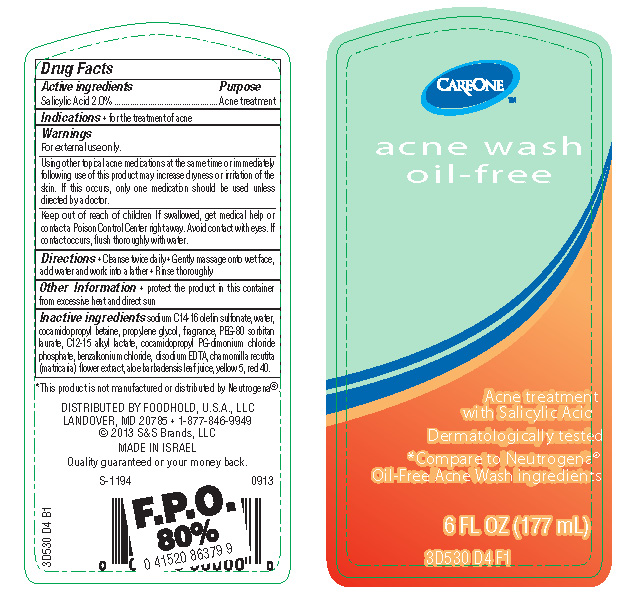 DRUG LABEL: Acne Wash Oil-Free
NDC: 41520-530 | Form: LIQUID
Manufacturer: American Sales Company
Category: otc | Type: HUMAN OTC DRUG LABEL
Date: 20130930

ACTIVE INGREDIENTS: SALICYLIC ACID 2 g/100 mL
INACTIVE INGREDIENTS: SODIUM C14-16 OLEFIN SULFONATE; WATER; COCAMIDOPROPYL BETAINE; PROPYLENE GLYCOL; SORBITAN MONOLAURATE; C12-15 ALKYL LACTATE; COCAMIDOPROPYL PG-DIMONIUM CHLORIDE PHOSPHATE; BENZALKONIUM CHLORIDE; EDETATE DISODIUM; CHAMOMILE; ALOE VERA LEAF; FD&C YELLOW NO. 5; FD&C RED NO. 40

CareOne Acne Wash Oil-Free

Active ingredient

Salicylic Acid 2.0%

Purpose

Acne treatment

Uses

for the treatment of acne

Warnings

For external use only.

Using other topical acne medications at the same time or immediately following use of this product may increase dryness or irritation of the skin. If this occurs, only one medication should be used unless directed by a doctor.

If swallowed, get medical help or contact a Poison Control Center right away. Avoid contact with eyes, If contact occurs, flush thoroughly with water.

Directions

Cleanse twice daily

Gently massage onto wet face, add water and work into a lather

Rinse thoroughly

Other information

protect the product in this container from excessive heat and direct sun

Inactive ingredients

sodium C14-16 olefin sulfonate, water, cocamidopropyl betaine, propylene glycol, fragrance, PEG-80 sorbitan laurate, C12-15 alkyl lactate, cocamidopropyl PG-dimonium chloride phosphate, bezalkonium chloride, disodium EDTA, chamomilla recutita (matricaria) flower extract, aloe barbadensis leaf juice, yellow 5, red 40.

Package/Label Principal Display Panel

CareOne acne wash oil-free

Acne treatment with Salicylic Acid

Dermatologically tested

*Compare to Neutrogena© Oil-Free Acne Wash ingredients

6 FL OZ (177 mL)

3D530 D4 F1

*This product is not manufactured or distributed by Neutrogena©

DISTRIBUTED BY FOODHOLD, U.S.A., LLC
LANDOVER, MD 20785 1-877-846-9949
© 2013 S&S Brands, LLC
MADE IN ISRAEL

Quality guaranteed or your money back.

Bottle Label